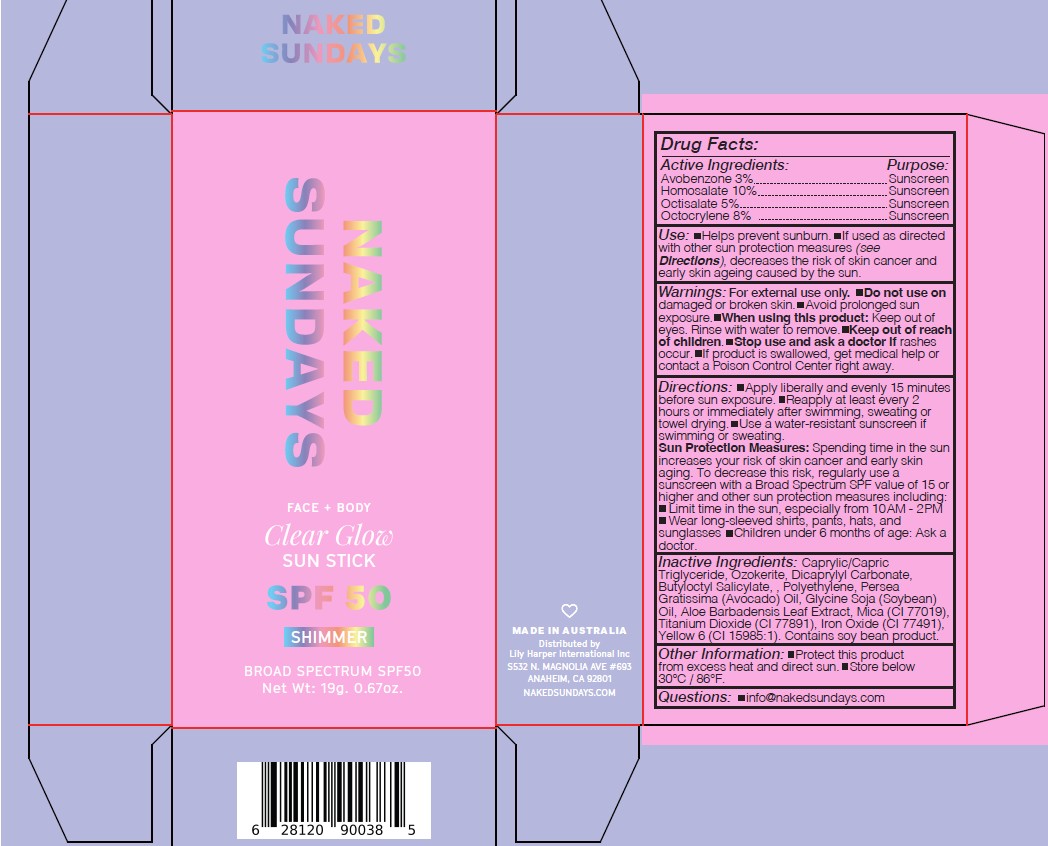 DRUG LABEL: Naked Sundays Face Body Clear Glow Sunstick SPF50 SHIMMER Broad Spectrum SPF50 19g
NDC: 81104-107 | Form: STICK
Manufacturer: NAKED SUNDAYS PTY LTD
Category: otc | Type: HUMAN OTC DRUG LABEL
Date: 20250322

ACTIVE INGREDIENTS: OCTISALATE 5 g/100 g; AVOBENZONE 3 g/100 g; OCTOCRYLENE 8 g/100 g; HOMOSALATE 10 g/100 g
INACTIVE INGREDIENTS: GLYCINE SOJA (SOYBEAN) OIL; DICAPRYLYL CARBONATE; FD&C YELLOW NO. 6 ALUMINUM LAKE; ALOE BARBADENSIS LEAF; TITANIUM DIOXIDE; CERESIN; PERSEA GRATISSIMA (AVOCADO) OIL; MICA; CAPRYLIC/CAPRIC TRIGLYCERIDE; BUTYLOCTYL SALICYLATE; POLYETHYLENE; BROWN IRON OXIDE

Naked Sundays Face + Body Clear Glow Sunstick SPF50 SHIMMER Broad Spectrum SPF50 19g

ACTIVE INGREDIENT

Avobenzone 3%
Homosalate 10%
Octisalate 5%
Octocrylene 8%

PURPOSE

SUNSCREEN

INACTIVE INGREDIENT

INACTIVE INGREDIENTS: Aloe Barbadensis Leaf Extract, Butyloctyl Salicylate, Caprylic/Capric Triglyceride, Dicaprylyl Carbonate, FD&C Yellow 6 Lake (CI 15985:1), Glycine Soja (Soybean) Oil, Iron Oxides (CI 77491), Mica, Ozokerite, Persea Gratissima (Avocado) Oil, Polyethylene, Titanium Dioxide (CI 77891)

INDICATIONS AND USAGE

Use: Helps prevent sunburn. If used as directed
with other sun protection measures (see
Directions), decreases the risk of skin cancer and
early skin ageing caused by the sun

DOSAGE AND ADMINISTRATION

Directions: Apply liberally and evenly 15 minutes
before sun exposure. Reapply at least every 2
hours or immediately after swimming, sweating or
towel drying. Use a water-resistant sunscreen if
swimming or sweating.

WARNINGS

Warnings: For external use only. Do not use on
damaged or broken skin. Avoid prolonged sun
exposure. When using this product: Keep out of
eyes. Rinse with water to remove. Keep out of reach
of children. Stop use and ask a doctor if rashes
occur. If product is swallowed, get medical help or
contact a Poison Control Center right away.

Keep out of reach
of children. Stop use and ask a doctor if rashes
occur.

OTHER SAFETY INFORMATION

Sun Protection Measures: Spending time in the sun
increases your risk of skin cancer and early skin
aging. To decrease this risk, regularly use a
sunscreen with a Broad Spectrum SPF value of 15 or
higher and other sun protection measures including:
Limit time in the sun, especially from 10AM - 2PM
Wear long-sleeved shirts, pants, hats, and
sunglasses Children under 6 months of age: Ask a
doctor.

Other Information: Protect this product
from excess heat and direct sun. Store below
30°C / 86°F.

Questions: info@nakedsundays.com